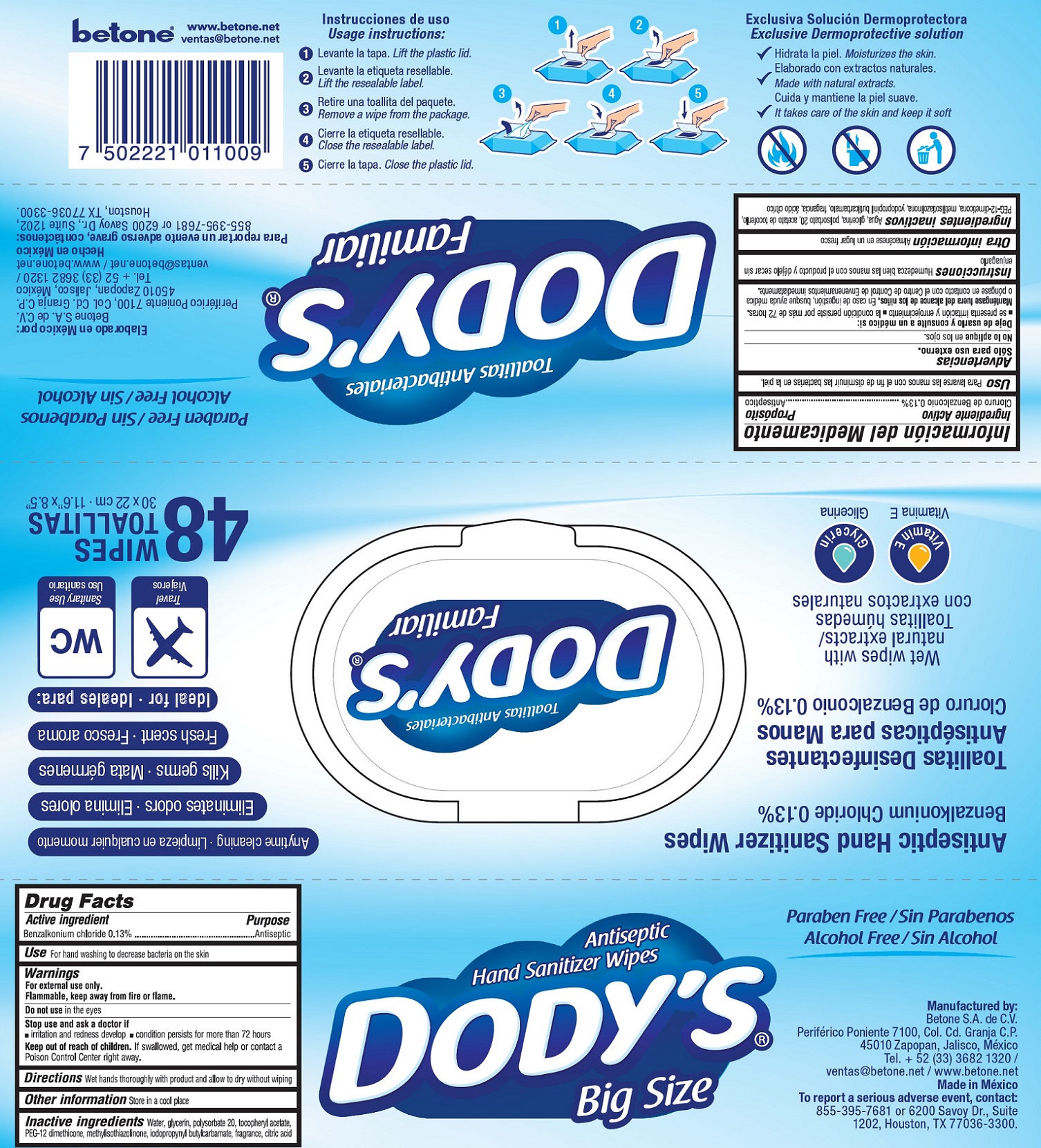 DRUG LABEL: DODYS
NDC: 77824-000 | Form: CLOTH
Manufacturer: Betone, S.A. de C.V.
Category: otc | Type: HUMAN OTC DRUG LABEL
Date: 20200623

ACTIVE INGREDIENTS: BENZALKONIUM CHLORIDE 1.3 mg/1 g
INACTIVE INGREDIENTS: WATER; GLYCERIN; POLYSORBATE 20; .ALPHA.-TOCOPHEROL ACETATE; PEG-12 DIMETHICONE; METHYLISOTHIAZOLINONE; IODOPROPYNYL BUTYLCARBAMATE; CITRIC ACID MONOHYDRATE

DODYS

Active ingredient

Benzalkonium chloride 0.13%

Purpose

Antiseptic

Use

For hand washing to decrease bacteria on the skin

Warnings

For external use only.

Flammable, keep away from fire or flame.

Do not use

in the eyes

Stop use and ask a doctor if

- irritation and redness develop
- condition persists for more than 72 hours

Keep out of reach of children.

If swallowed, get medical help or contact a Poison Control Center right away.

Directions

Wet hands thoroughly with product and allow to dry without wiping

Other information

Store in a cool place

Inactive ingredients

Water, glycerin, polysorbate 20, tocopheryl acetate, PEG-12 dimethicone, methylisothiazolinone, iodopropynyl butylcarbamate, fragrance, citric acid